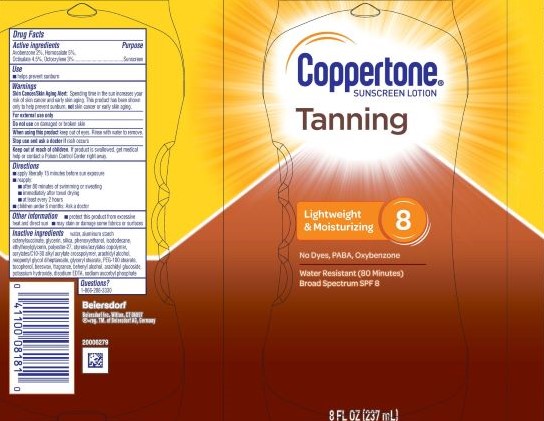 DRUG LABEL: Coppertone Tanning Sunscreen SPF 8
NDC: 66800-4086 | Form: LOTION
Manufacturer: Beiersdorf Inc
Category: otc | Type: HUMAN OTC DRUG LABEL
Date: 20251231

ACTIVE INGREDIENTS: OCTOCRYLENE 3 g/100 g; AVOBENZONE 2 g/100 g; OCTISALATE 4.5 g/100 g; HOMOSALATE 5 g/100 g
INACTIVE INGREDIENTS: ALUMINUM STARCH OCTENYLSUCCINATE; POTASSIUM HYDROXIDE; WATER; GLYCERIN; FRAGRANCE FLORAL ORC0902236; ISODODECANE; ETHYLHEXYLGLYCERIN; PHENOXYETHANOL; POLYESTER-7; DOCOSANOL; STYRENE/ACRYLAMIDE COPOLYMER (MW 500000); SILICON DIOXIDE; ACRYLATES CROSSPOLYMER-6; ARACHIDYL GLUCOSIDE; DISODIUM EDTA-COPPER; SODIUM ASCORBYL PHOSPHATE; PEG-100 STEARATE; ARACHIDYL ALCOHOL; NEOPENTYL GLYCOL DIHEPTANOATE; GLYCERYL STEARATE SE; SYNTHETIC BEESWAX

Tanning Lotion SPF 8

Active ingredients

Avobenzone 2%, Homosalate 5%, Octisalate 4.5%, Octocrylene 3%

Purpose

Sunscreen

Use

■ helps prevent sunburn

Warnings

Skin Cancer/Skin Aging Alert:Spending time in the sun increases your risk of skin cancer and early skin aging. This product has been shown only to help prevent sunburn, not skin cancer or early skin aging.

For external use only

Do not useon damaged or broken skin

WHEN USING

When using this productkeep out of eyes. Rinse with water to remove.

Stop use and ask a doctor ifrash occurs

Keep out of reach of children.If product is swallowed, get medical help or contact a Poison Control Center right away.

Directions

■ apply liberally 15 minutes before sun exposure

■ reapply:

■ after 80 minutes of swimming or sweating

■ immediately after towel drying

■ at least every 2 hours

■ children under 6 months: Ask a doctor

Other information

■ protect this product from excessive heat and direct sun

■ may stain or damage some fabrics or surfaces

Inactive ingredients

water, aluminum starch octenylsuccinate, glycerin, silica, phenoxyethanol, isododecane, ethylhexylglycerin, polyester-27, styrene/acrylates copolymer, acrylates/C10-30 alkyl acrylate crosspolymer, arachidyl alcohol, neopentyl glycol diheptanoate, glyceryl stearate, PEG-100 stearate, beeswax, fragrance, behenyl alcohol, arachidyl glucoside, potassium hydroxide, disodium EDTA, sodium ascorbyl phosphate

Questions

1-866-288-3330

PACKAGE LABEL

Coppertone®Sunscreen Lotion

Tanning

Lightweight & Moisturizing 8

No Dyes, PABA, Oxybenzone

Water Resistant (80 Minutes)

Broad Spectrum SPF 8

8 FL OZ (237 mL)